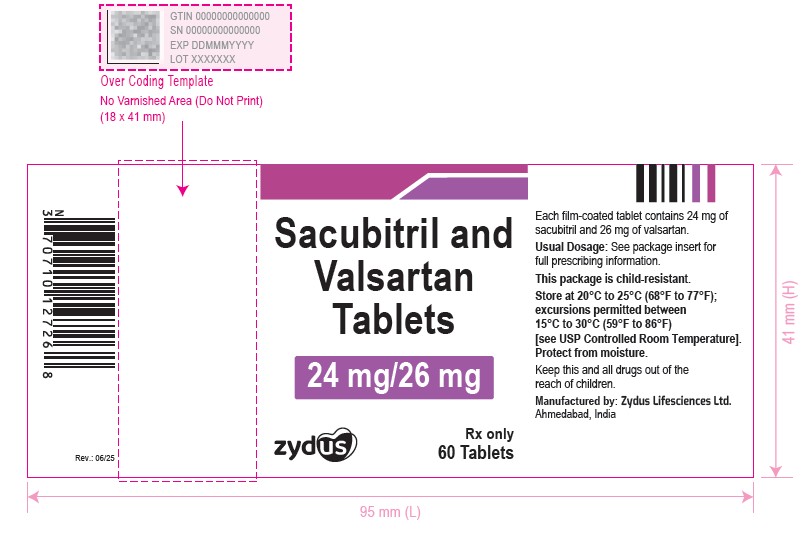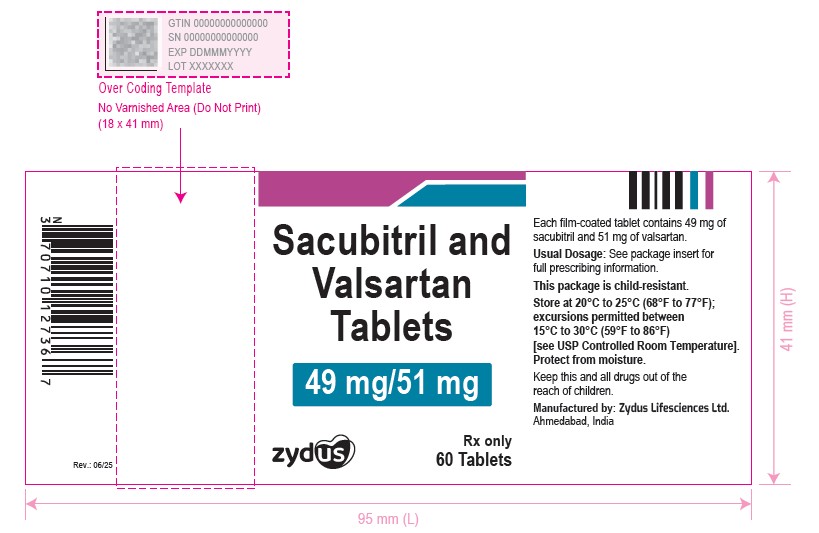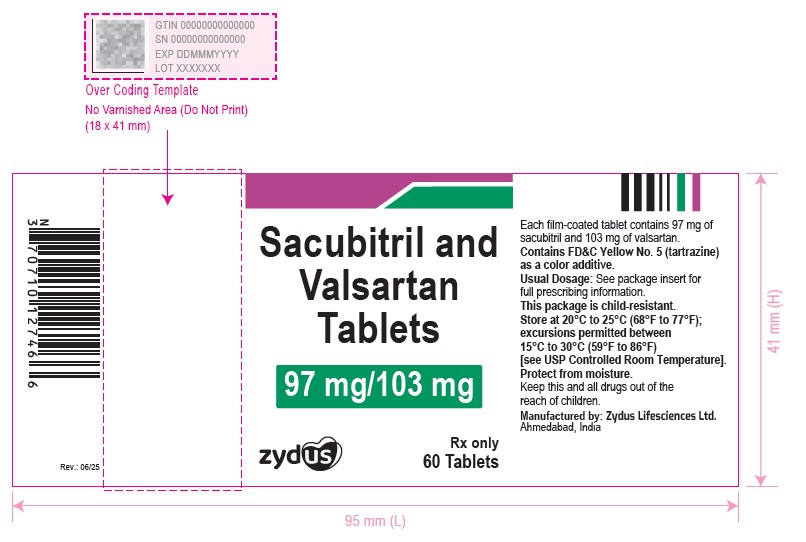 DRUG LABEL: sacubitril and valsartan
NDC: 70771-1921 | Form: TABLET
Manufacturer: Zydus Lifesciences Limited
Category: prescription | Type: HUMAN PRESCRIPTION DRUG LABEL
Date: 20250708

ACTIVE INGREDIENTS: SACUBITRIL 24 mg/1 1; VALSARTAN 26 mg/1 1
INACTIVE INGREDIENTS: CROSPOVIDONE (15 MPA.S AT 5%); HYDROXYPROPYL CELLULOSE, LOW SUBSTITUTED; HYPROMELLOSE 2910 (6 MPA.S); MICROCRYSTALLINE CELLULOSE 101; MICROCRYSTALLINE CELLULOSE 102; POLYETHYLENE GLYCOL 8000; SILICON DIOXIDE; SODIUM STEARYL FUMARATE; TITANIUM DIOXIDE

Sacubitril and Valsartan Tablets

PACKAGE LABEL.PRINCIPAL DISPLAY PANEL

NDC 70771-1921-6

Sacubitril and valsartan tablets, 24 mg/26 mg

60 Tablets

Rx only

NDC 70771-1922-6

Sacubitril and valsartan tablets, 49 mg/51 mg

60 Tablets

Rx only

NDC 70771-1923-6

Sacubitril and valsartan tablets, 97 mg/103 mg

60 Tablets

Rx only